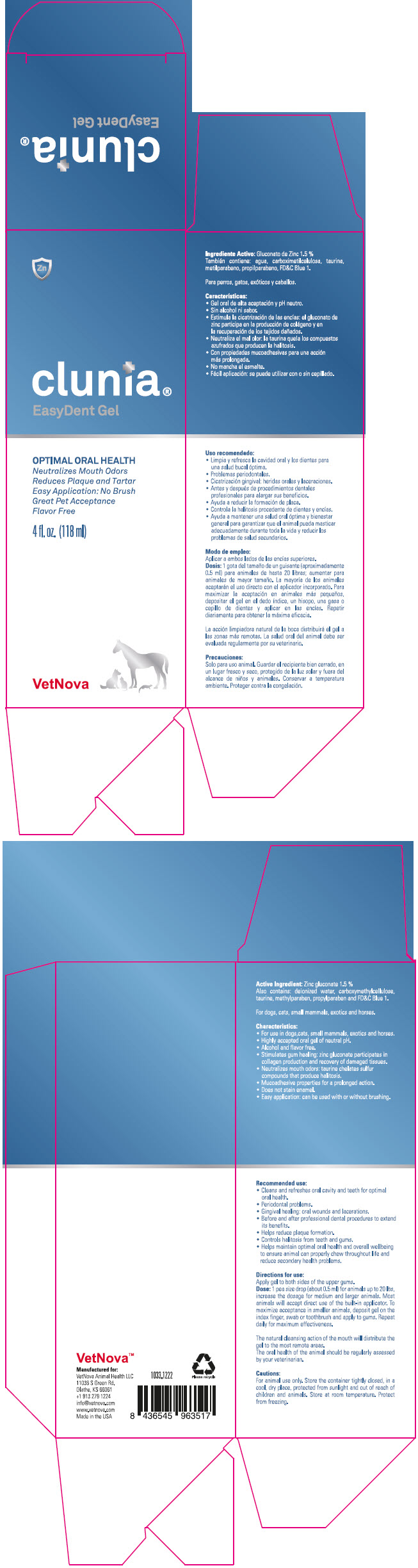 DRUG LABEL: Clunia EasyDent
NDC: 86145-500 | Form: LIQUID
Manufacturer: Vetnova Animal Health LLC
Category: animal | Type: OTC ANIMAL DRUG LABEL
Date: 20251118

ACTIVE INGREDIENTS: zinc gluconate 15 mg/1 mL
INACTIVE INGREDIENTS: Carboxymethylcellulose; Lysine; taurine; Water; Methylparaben; Propylparaben

Clunia® EasyDent Gel

Active Ingredient: Zinc gluconate 1.5 %

Also contains deionized water, carboxymethylcellulose, taurine, methylparaben, propylparaben, and FD&C Blue 1.

For dogs, cats small mammals, exotics and horses.

VETERINARY INDICATIONS

Characteristics:

- For use in dogs, cats, small mammals, exotics and horses
- Highly accepted oral gel of neutral pH.
- Alcohol and flavor free.
- Stimulates gum healing zinc gluconate participates in collagen production and recovery of damaged tissues.
- Neutralizes mouth odors: taurine chelates sulfur compounds that produce halitosis
- Mucoadhesive properties for prolonged action
- Does not stain enamel
- Easy application: can be used with or without brushing

INDICATIONS AND USAGE

Recommended use:

- Cleans and refreshes oral cavity and teeth for optimal oral health.
- Periodontal problems.
- Gingival healing: oral wounds and lacerations.
- Before and after professional dental procedures to extend its benefits
- Helps reduce plaque formation.
- Controls halitosis from teeth and gums.
- Helps maintain optimal oral health and overall wellbeing to ensure animal can properly chew throughout life and reduce secondary health problems.

DOSAGE AND ADMINISTRATION

Directions for use:

Apply gel to both sides of the upper gums.

Dose: 1 pea size drop (about 0.5 ml)for animals up to 20 lbs, increase the dosage for medium and larger animals. Most animals will accept direct use of the built-in applicator. To maximize acceptance in smaller animals, deposit gel on the index finger, swab or toothbrush and apply to gums. Repeat daily for maximum effectiveness.

The natural cleansing action of the mouth will distribute the gel to the most remote areas.

The oral health of the animal should be regularly assessed by your veterinarian.

PRECAUTIONS

Cautions:

For animal use only. Store the container tightly closed, in a cool, dry place, protected from sunlight and out of reach of children and animals. Store at room temperature. Protect from freezing.

Manufactured for:
VetNova Animal Health LLC
11036 S Green Rd.
Olathe, KS 66061
+1 913 279 1224
info@vetnova.com
www.vetnova.com
Made in the USA

1033.1222

Please recycle

PRINCIPAL DISPLAY PANEL - 118 ml Bottle Box

clunia®
EasyDent Gel

OPTIMAL ORAL HEALTH
Neutralizes Mouth Odors
Reduces Plaque and Tartar
Easy Application: No Brush
Great Pet Acceptance
Flavor Free

4fl. oz. (118 ml)

VetNova